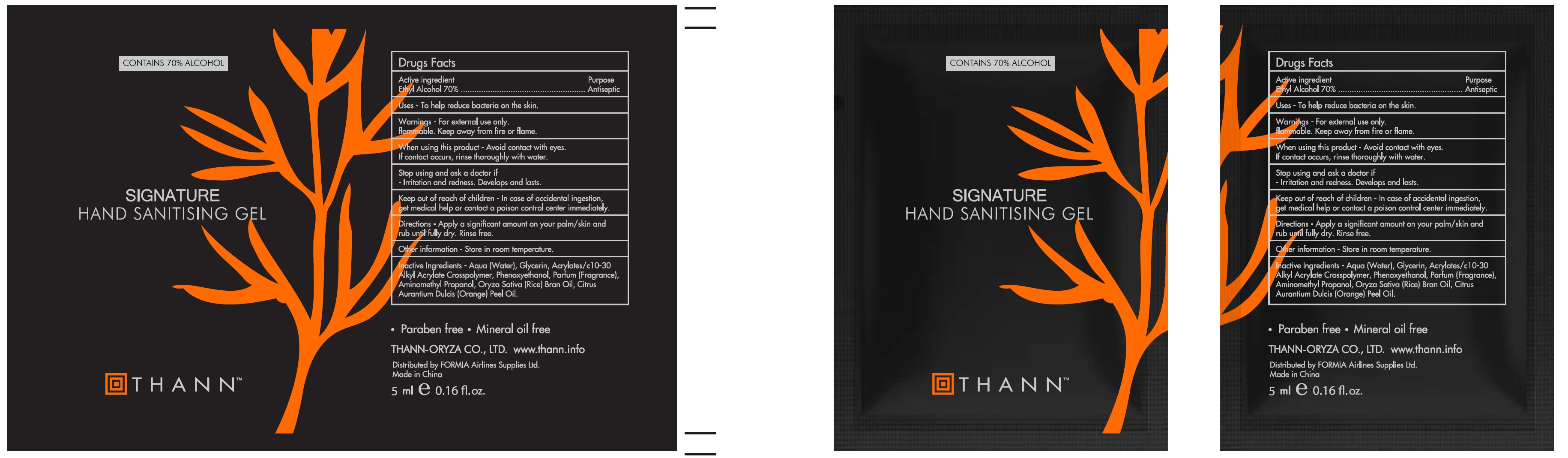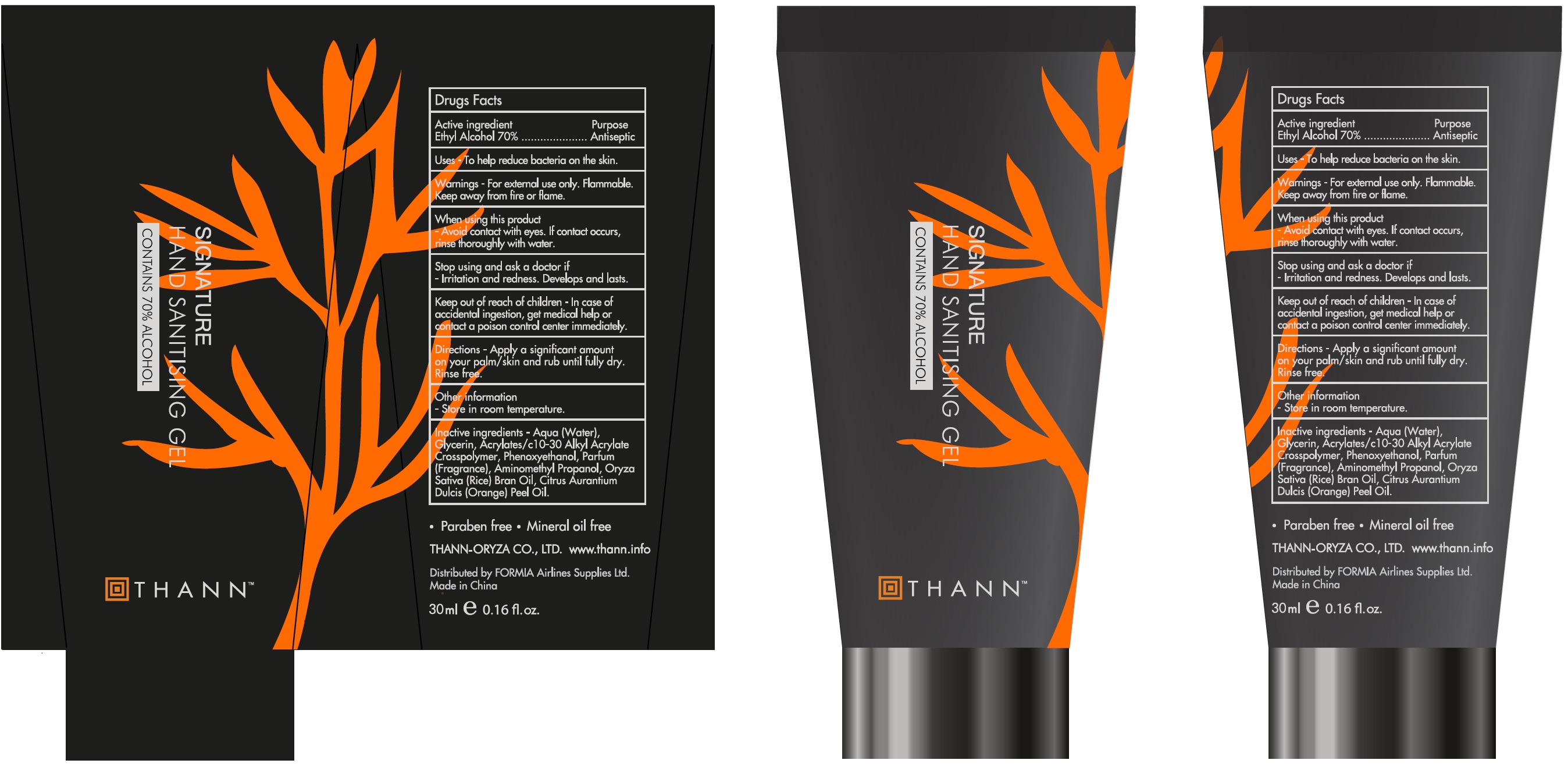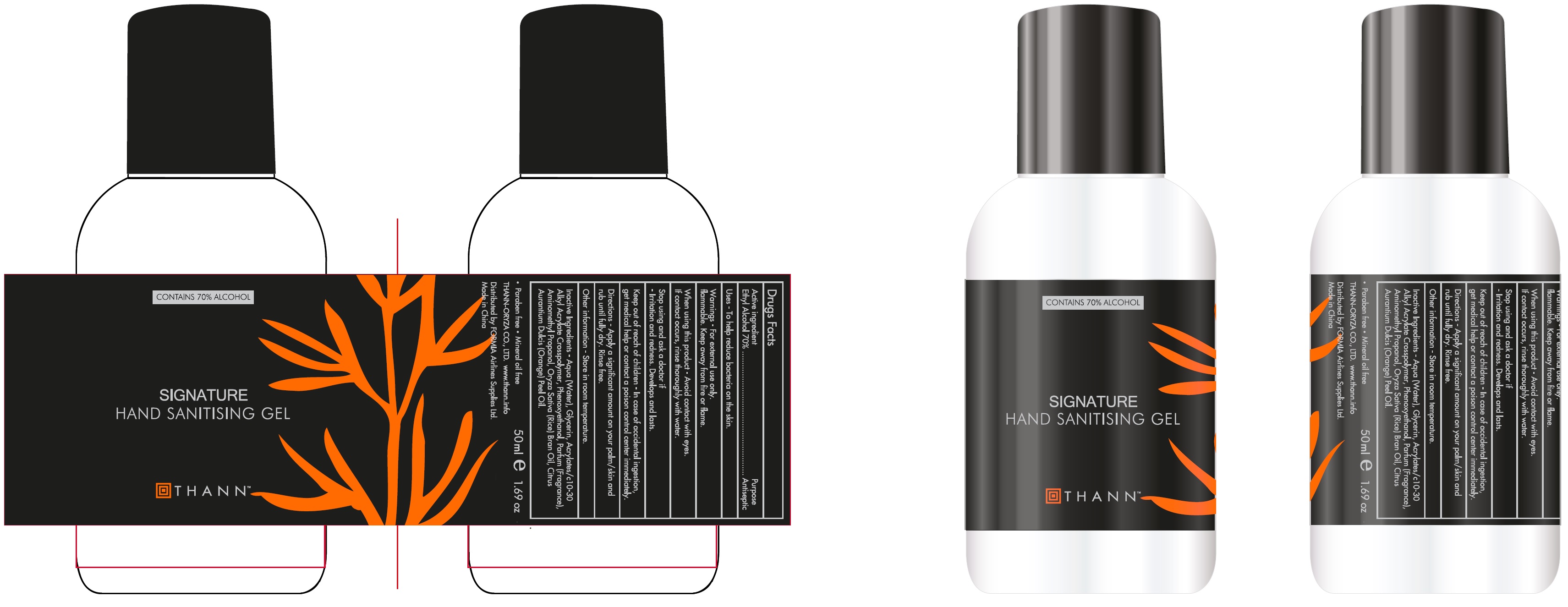 DRUG LABEL: Thann Signature Hand Sanitising
NDC: 79940-001 | Form: GEL
Manufacturer: FORMIA Airline Supplies Ltd
Category: otc | Type: HUMAN OTC DRUG LABEL
Date: 20201029

ACTIVE INGREDIENTS: ALCOHOL 0.7 mL/1 mL
INACTIVE INGREDIENTS: WATER; GLYCERIN; CARBOMER INTERPOLYMER TYPE A (ALLYL SUCROSE CROSSLINKED); PHENOXYETHANOL; AMINOMETHYLPROPANOL; RICE BRAN OIL; ORANGE OIL

Thann Signature Hand Sanitising Gel

Active ingredient

Ethyl Alcohol 70%

Purpose

Antiseptic

Uses

- To help reduce bacteria on the skin.

Warnings

-For external use only.
Flammable. Keep away from fire or flame.

When using this product

-Avoid contact with eyes. If contact occurs, rinse thoroughly with water.

Stop using and ask a doctor if

-Irritation and redness. Develops and lasts.

Keep out of reach of children

-In case of accidental ingestion, get medical help or contact a poison control center immediately.

Directions

-Apply a significant amount on your palm/ skin and rub until fully dry. Rinse free.

Other information

-Store in room temperature.

Inactive Ingredients

-Aqua (Water), Glycerin, Acrylates/c10-30 Alkyl Acrylate Crosspolymer, Phenoxyethanol, Parfum (Fragrance), Aminomethyl Propanol, Oryza Sativa (Rice) Bran Oil, Citrus Aurantium Dulcis (Orange) Peel Oil.